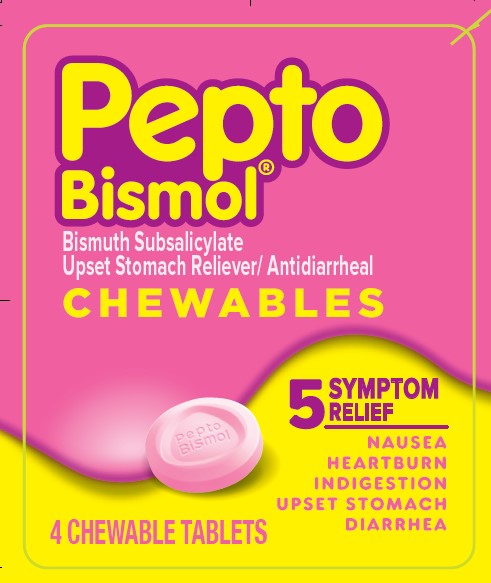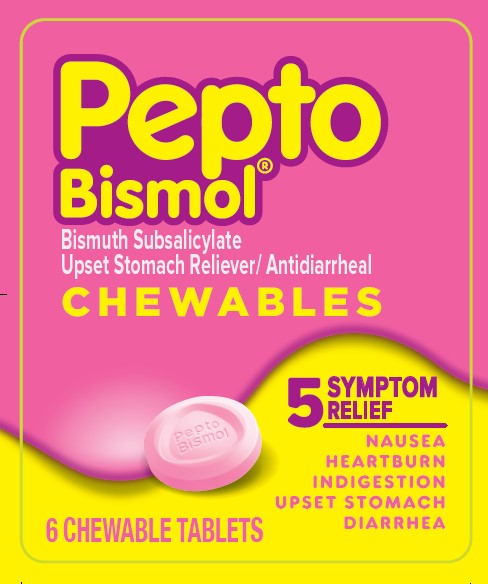 DRUG LABEL: Pepto Bismol
NDC: 29485-1531 | Form: TABLET, CHEWABLE
Manufacturer: Lil' Drug Store Products, Inc.
Category: otc | Type: HUMAN OTC DRUG LABEL
Date: 20230719

ACTIVE INGREDIENTS: BISMUTH SUBSALICYLATE 262 mg/1 1
INACTIVE INGREDIENTS: MANNITOL; TALC; CALCIUM CARBONATE; MAGNESIUM STEARATE; POVIDONE, UNSPECIFIED; D&C RED NO. 27 ALUMINUM LAKE; SACCHARIN SODIUM

Pepto Bismol

Active Ingredient(in each tablet)

Bismuth subsalicylate 262 mg

Purpose

Upset stomach reliever and antidiarrheal

Uses

relieves

• travelers' diarrhea

• diarrhea

• upset stomach due to overindulgence in food and drink, including:

• heartburn

• indigestion

• nausea

• gas

• belching

• fullness

Warnings

Reye's syndrome

Children and teenagers who have or are recovering from chicken pox or flu-like symptoms should not use this product. When using this product, if changes in behavior with nausea and vomiting occur, consult a doctor because these symptoms could be an early sign of Reye's syndrome, a rare but serious illness.

Allergy alert

Contains salicylate. Do not take if you are

- allergic to salicylates (including aspirin)
- taking other salicylate products

Do not use if you have

- an ulcer
- a bleeding problem
- bloody or black stool

Ask a doctor before use if you have

- fever
- mucus in the stool

Ask a doctor or pharmacist before use if you are taking any drug for

- anticoagulation (thinning the blood)
- diabetes
- gout
- arthritis

When using this product a temporary, but harmless, darkening of the stool and/or
tongue may occur

Stop use and ask a doctor if

- symptoms get worse
- ringing in the ears or loss of hearing occurs
- diarrhea lasts more than 2 days

PREGNANCY OR BREAST FEEDING

If pregnant or breast feeding, ask a health professional before use.

Keep out of reach of children. In case of overdose, get medical help or contact a Poison Control Center right away.

Directions

- chew or dissolve in mouth
- adults and children 12 years and over: 2 tablets (1 dose) every 1/2 hour or 4 tablets (2 doses) every hour as needed for diarrhea
- 2 tablets (1 dose) every ½ hour as needed for overindulgence (upset stomach, heartburn, indigestion, nausea)
- do not exceed 8 doses (16 tablets) in 24 hours
- use until diarrhea stops but not more than 2 days
- children under 12 years: ask a doctor
- drink plenty of clear fluids to help prevent dehydration caused by diarrhea

Other Information

- each tablet contains: calcium 140 mg, magnesium 9 mg
- salicylate 99 mg
- low sodium
- avoid excessive heat (over 104°F or 40°C)

Inactive Ingredients

adipic acid, calcium carbonate, D&C Red No. 27 aluminum lake, FD&C Red No. 40 aluminum lake, flavor, magnesium stearate, mannitol, povidone, saccharin sodium, talc

Questions?

1-800-717-3786

PRODUCT REPACKAGED AND DISTRIBUTED WITH PERMISSION OF MANUFACTURER BY:

Convenience Valet® Glendale Heights, IL 60139 1-800-351-2000 (8:30 AM - 5:00 PM CST)

PACKAGE LABEL

Pepto Bismol
Bismuth Subsalicylate
Upset Stomach Reliever/Antidiarrheal

CHEWABLES

5 SYMPTOM RELIEF

NAUSEA

HEARTBURN

INDIGESTION

UPSET STOMACH

DIARRHEA

4 CHEWABLE TABLETS

PACKAGE LABEL

Pepto Bismol
Bismuth Subsalicylate
Upset Stomach Reliever/Antidiarrheal

CHEWABLES

5 SYMPTOM RELIEF

NAUSEA

HEARTBURN

INDIGESTION

UPSET STOMACH

DIARRHEA

6 CHEWABLE TABLETS